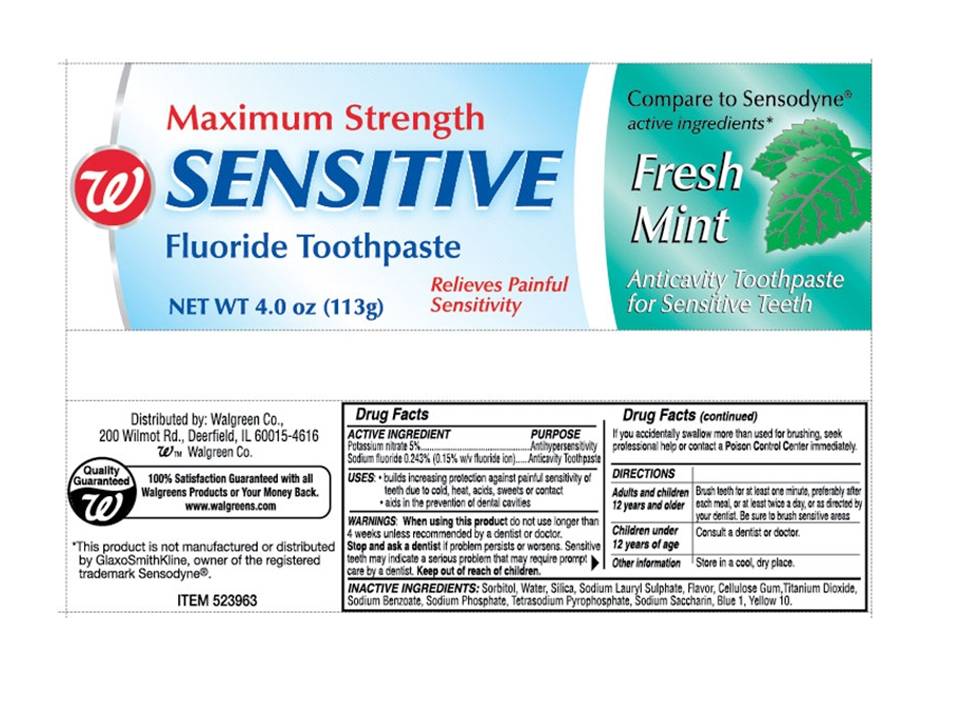 DRUG LABEL: Walgreens Maximum Strength Sensitive Fluoride
NDC: 0363-0631 | Form: PASTE
Manufacturer: Walgreens
Category: otc | Type: HUMAN OTC DRUG LABEL
Date: 20110415

ACTIVE INGREDIENTS: POTASSIUM NITRATE 5 mg/1 g; SODIUM FLUORIDE 2.43 mg/1 g
INACTIVE INGREDIENTS: SORBITOL; WATER; SILICON DIOXIDE; SODIUM LAURYL SULFATE; CARBOXYMETHYLCELLULOSE SODIUM; TITANIUM DIOXIDE; SODIUM BENZOATE; SODIUM PHOSPHATE; SODIUM PYROPHOSPHATE; SACCHARIN SODIUM; FD&C BLUE NO. 1; D&C YELLOW NO. 10

Walgreen Maximum Strength Sensitive Toothpaste

Active Ingredient

Potassium nitrate 5%........................................... Antihypersensitivity

Sodium Fluoride 0.243% (0.15% w/v fluoride ion).... Anticavity toothpaste

When using this product do not use longer than 4 weeks unless recommended by a dentist or doctor. Stop and ask a dentist if problems persists or worsens. Sensitive teeth may indicate a serious problem that may require prompt care by a dentist. Keep out of reach of children. If you accidentally swallow more that used for brushing seek professional help or contact a Poison Control Center immediately.

Directions

Adults and children Brush teeth for at least one minute, preferably after
12 years and older each meal, or at least twice a day or as directed by
your dentist. Be sure to brush sensitive areas.
Children under Consult a dentist or doctor
12 years of age
Other information Store in a cool, dry place.

USE

- Builds increasing protection against painful sensitivity of teeth due to cold, heat, acids, sweets or contact
- Aids in the prevention of dental cavities

Inactive Ingredients

Sorbitol,Water, Silica, Sodium Lauryl Sulphate, Flavor, Cellulose Gum,Titanium Dioxide, Sodium Benzoate, Sodium Phosphate, Tetrasodium Pyrophosphate, Sodium Saccharin, FDC Blue No. 1, DC Yellow No.10